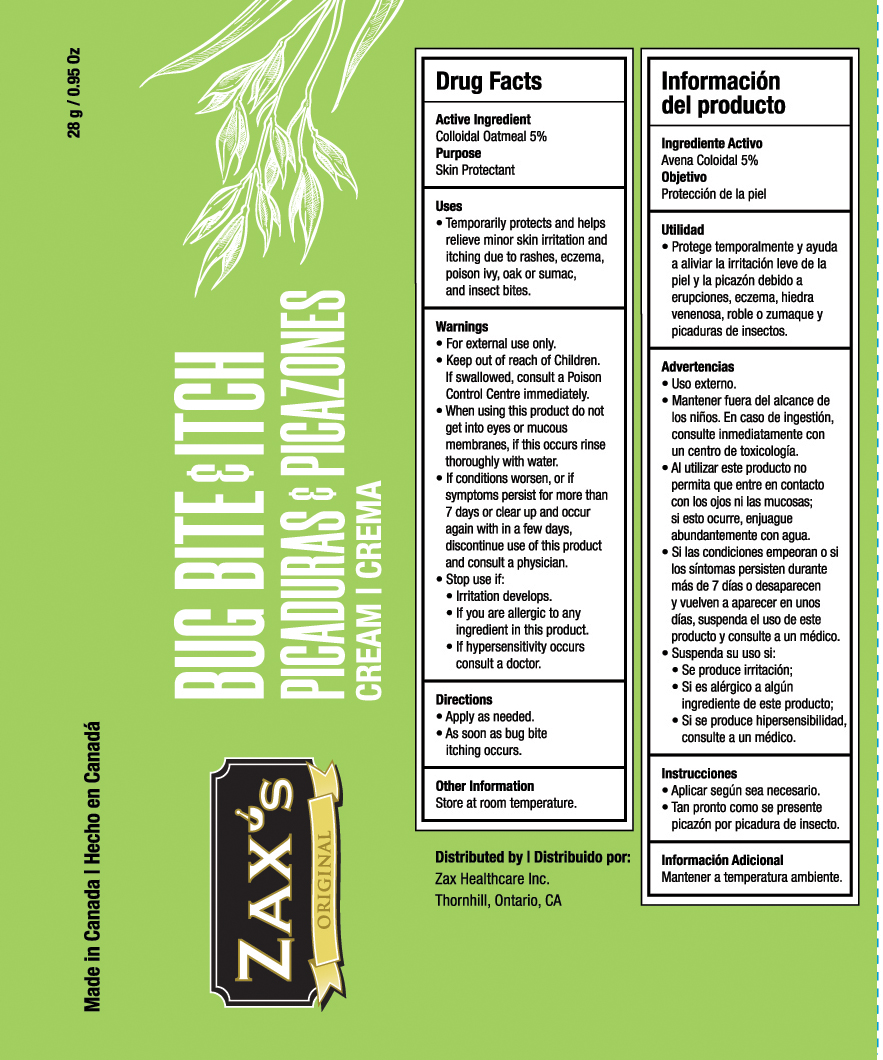 DRUG LABEL: Zaxs Original Bug Bite and Itch
NDC: 82186-155 | Form: CREAM
Manufacturer: Zax Healthcare Inc.
Category: otc | Type: HUMAN OTC DRUG LABEL
Date: 20241012

ACTIVE INGREDIENTS: OATMEAL 50 mg/1 g
INACTIVE INGREDIENTS: ARNICA MONTANA FLOWER; POLYOXYL 20 CETOSTEARYL ETHER; COCONUT OIL; MENTHOL; PHENOXYETHANOL; SORBIC ACID; TOCOPHEROL; CETOSTEARYL ALCOHOL; CITRIC ACID MONOHYDRATE; ALCOHOL; CAPRYLYL GLYCOL; CETYL ALCOHOL; GLYCERIN; GLYCERYL MONOSTEARATE; SOYBEAN OIL; WITCH HAZEL; MELALEUCA ALTERNIFOLIA (TEA TREE) LEAF OIL; WATER; XANTHAN GUM

Zax's Original Bug Bite & Itch Cream

Drug Facts

Colloidal Oatmeal 5%

Active Ingredient

Colloidal Oatmeal 5%

Purpose

Skin Protectant

Uses

Temporarily protects and helps relieve minor skin irritation and itching due to rashes, eczema, poison ivy, oak or sumac, and insect bites.

Warnings

•For external use only.

•When using this product do not get into eyes or mucous membranes. If this occurs, rinse thoroughly with water.

•If conditions worsen, or if symptoms persist for more than 7 days or clear up and occur again within a few days, discontinue use of this product and consult a physician.

•Stop use if:

•irritation develops.

•If you are allergic to any ingredient in this product.

•If hypersensitivity occurs consult a doctor

Keep out of the reach of children. If swallowed, consult a Poison Control Centre immediately.

Directions

•Apply as needed.

•As soon as bug bite itching occurs.

Inactive Ingredients

Alcohol

Arnica Montana Flower Extract

Caprylic/Capric Glycerides

Caprylyl Glycol

Ceteareth-20

Cetearyl Alcohol

Cetyl Alcohol

Citric Acid

Cocos Nucifera (Coconut) Oil

Glycerin

Glyceryl Stearate

Glycine Soja (Soybean) Oil

Hamamelis Virginiana (Witch Hazel) Bark/Leaf/Twig Extract

Melaleuca Alternifolia (Tea Tree) Leaf Oil

Menthol

Phenoxyethanol

Sorbic Acid

Tocopherol

Water

Xanthum Gum

Other Information

Store at room temperature.